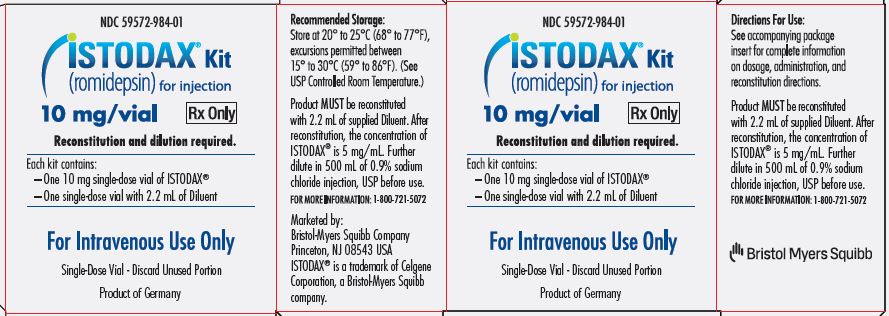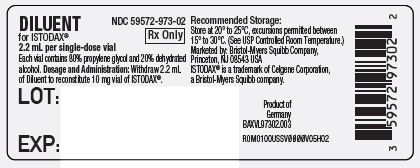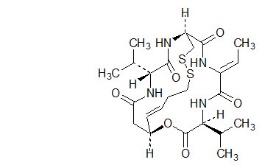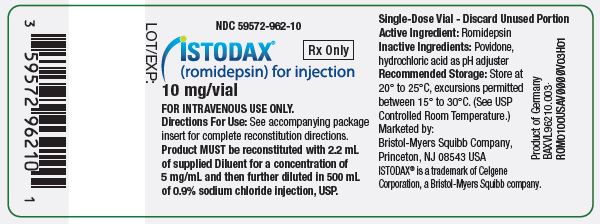 DRUG LABEL: ISTODAX
NDC: 59572-983 | Form: KIT | Route: INTRAVENOUS
Manufacturer: Celgene Corporation
Category: prescription | Type: HUMAN PRESCRIPTION DRUG LABEL
Date: 20230131

ACTIVE INGREDIENTS: ROMIDEPSIN 10 mg/2 mL
INACTIVE INGREDIENTS: POVIDONE, UNSPECIFIED; ALCOHOL; PROPYLENE GLYCOL

HIGHLIGHTS OF PRESCRIBING INFORMATION

These highlights do not include all the information needed to use ISTODAX safely and effectively. See full prescribing information for ISTODAX.
ISTODAX® (romidepsin) for injection, for intravenous use
Initial U.S. Approval: 2009

RECENT MAJOR CHANGES

Indications and Usage, Peripheral T-cell Lymphoma (1.2) Removed | 7/2021

1 INDICATIONS AND USAGE

ISTODAX is a histone deacetylase (HDAC) inhibitor indicated for the treatment of cutaneous T-cell lymphoma (CTCL) in adult patients who have received at least one prior systemic therapy (1).

2 DOSAGE AND ADMINISTRATION

- 14 mg/m^2 administered intravenously over a 4-hour period on days 1, 8, and 15 of a 28-day cycle. Repeat cycles every 28 days provided that the patient continues to benefit from and tolerates the drug (2.1).
- Discontinue or interrupt treatment (with or without dose reduction to 10 mg/m^2) to manage drug toxicity (2.2).
- Reduce starting dose in patients with moderate and severe hepatic impairment (2.3).

3 DOSAGE FORMS AND STRENGTHS

For injection: 10 mg of romidepsin as a lyophilized powder in single-dose vial for reconstitution (3).

4 CONTRAINDICATIONS

None (4).

5 WARNINGS AND PRECAUTIONS

- Myelosuppression: ISTODAX can cause thrombocytopenia, leukopenia (neutropenia and lymphopenia), and anemia; monitor blood counts during treatment with ISTODAX; interrupt and/or modify the dose as necessary (5.1).
- Infections: Fatal and serious infections. Reactivation of DNA viruses (Epstein Barr and hepatitis B). Consider monitoring and prophylaxis in patients with evidence of prior hepatitis B (5.2).
- Electrocardiographic (ECG) changes: Consider cardiovascular monitoring in patients with congenital long QT syndrome, a history of significant cardiovascular disease, and patients taking medicinal products that lead to significant QT prolongation. Ensure that potassium and magnesium are within the normal range before administration of ISTODAX (5.3).
- Tumor lysis syndrome: Patients with advanced stage disease and/or high tumor burden are at greater risk and should be closely monitored and appropriate precautions taken (5.4).
- Embryo-fetal toxicity: Can cause fetal harm. Advise females of reproductive potential and males with female partners of reproductive potential of potential risk to a fetus and to use effective contraception (5.5, 8.1, 8.3).

6 ADVERSE REACTIONS

The most common adverse reactions (≥30%), excluding laboratory abnormalities, are nausea, fatigue, infections, vomiting, anorexia, electrocardiogram ST-T wave changes, dysgeusia, constipation and pruritis. Grade 3‐4 laboratory abnormalities (≥10%) include lymphopenia, neutropenia, anemia and thrombocytopenia (6).

To report SUSPECTED ADVERSE REACTIONS, contact Bristol-Myers Squibb at 1-800-721-5072 or the FDA at 1-800-FDA-1088 or www.fda.gov/medwatch.

7 DRUG INTERACTIONS

- Carefully monitor prothrombin time (PT) and International Normalized Ratio (INR) in patients concurrently administered ISTODAX and warfarin or coumarin derivatives (7.1).
- Monitor for toxicities related to increased romidepsin exposure when co-administering romidepsin with strong CYP3A4 inhibitors (7.2).
- Avoid use with rifampin and strong CYP3A4 inducers (7.3).

FULL PRESCRIBING INFORMATION

1 INDICATIONS AND USAGE

ISTODAX is indicated for the treatment of cutaneous T-cell lymphoma (CTCL) in adult patients who have received at least one prior systemic therapy.

2 DOSAGE AND ADMINISTRATION

2.1 Dosage Information

The recommended dosage of romidepsin is 14 mg/m^2 administered intravenously over a 4-hour period on days 1, 8, and 15 of a 28-day cycle. Cycles should be repeated every 28 days provided that the patient continues to benefit from and tolerates the drug.

2.2 Dosage Modification

Nonhematologic toxicities except alopecia

- Grade 2 or 3 toxicity: Treatment with romidepsin should be delayed until toxicity returns to Grade 0-1 or baseline, then therapy may be restarted at 14 mg/m^2. If Grade 3 toxicity recurs, treatment with romidepsin should be delayed until toxicity returns to Grade 0-1 or baseline and the dose should be permanently reduced to 10 mg/m^2.
- Grade 4 toxicity: Treatment with romidepsin should be delayed until toxicity returns to Grade 0-1 or baseline, then the dose should be permanently reduced to 10 mg/m^2.
- Romidepsin should be discontinued if Grade 3 or 4 toxicities recur after dose reduction.

Hematologic toxicities

- Grade 3 or 4 neutropenia or thrombocytopenia: Treatment with romidepsin should be delayed until the specific cytopenia returns to ANC greater than or equal to 1.5×10^9/L and platelet count greater than or equal to 75×10^9/L or baseline, then therapy may be restarted at 14 mg/m^2.
- Grade 4 febrile (greater than or equal to 38.5ºC) neutropenia or thrombocytopenia that requires platelet transfusion: Treatment with romidepsin should be delayed until the specific cytopenia returns to less than or equal to Grade 1 or baseline, and then the dose should be permanently reduced to 10 mg/m^2.

2.3 Dosage in Patients with Hepatic Impairment

For patients with moderate or severe hepatic impairment, reduce the starting dose of ISTODAX as shown in Table 1 and monitor for toxicities more frequently. Dosage adjustment is not required for patients with mild hepatic impairment.

Table 1: Recommendations for Starting Dose in Patients with Moderate and Severe Hepatic Impairment
Hepatic Impairment | Bilirubin Levels | ISTODAX Dose
Moderate | greater than 1.5 × ULN to less than or equal to 3 × ULN | 7 mg/m^2
Severe | greater than 3 × ULN | 5 mg/m^2
ULN=Upper limit of normal.

2.4 Instructions for Preparation and Intravenous Administration

ISTODAX is a hazardous drug. Use appropriate handling procedures.^1

ISTODAX must be reconstituted with the supplied diluent and further diluted with 0.9% Sodium Chloride Injection, USP, before intravenous infusion.

ISTODAX and diluent vials contain an overfill to ensure the recommended volume can be withdrawn at a concentration of 5 mg/mL.

- Each 10 mg single-dose vial of ISTODAX must be reconstituted with 2.2 mL of the supplied diluent.
- With a suitable syringe, aseptically withdraw 2.2 mL from the supplied diluent vial, and slowly inject it into the ISTODAX (romidepsin) for injection vial. Swirl the contents of the vial until there are no visible particles in the resulting solution. The reconstituted solution will contain ISTODAX 5 mg/mL. The reconstituted ISTODAX vial will contain 2 mL of deliverable volume of drug product. The reconstituted ISTODAX solution is chemically stable for up to 8 hours at room temperature.
- Extract the appropriate amount of ISTODAX from the vials to deliver the desired dose, using proper aseptic technique. Before intravenous infusion, further dilute ISTODAX in 500 mL 0.9% Sodium Chloride Injection, USP.
- Infuse over 4 hours.

The diluted solution is compatible with polyvinyl chloride (PVC), ethylene vinyl acetate (EVA), polyethylene (PE) infusion bags as well as glass bottles, and is chemically stable for up to 24 hours when stored at room temperature. However, it should be administered as soon after dilution as possible.

Parenteral drug products should be inspected visually for particulate matter and discoloration before administration, whenever solution and container permit.

3 DOSAGE FORMS AND STRENGTHS

For Injection: 10 mg of romidepsin as a lyophilized white powder in a single-dose vial for reconstitution and further dilution.

4 CONTRAINDICATIONS

None.

5 WARNINGS AND PRECAUTIONS

5.1 Myelosuppression

Treatment with ISTODAX can cause thrombocytopenia, leukopenia (neutropenia and lymphopenia), and anemia. Monitor blood counts regularly during treatment with ISTODAX and modify the dose as necessary [see Dosage and Administration (2.2) and Adverse Reactions (6.1)].

5.2 Infections

Fatal and serious infections have been reported in clinical trials of ISTODAX, including pneumonia, sepsis, and viral reactivation, including reactivation of Epstein Barr and hepatitis B viruses. These infections can occur during and following treatment. The risk of life-threatening infections may be greater in patients with a history of prior treatment with monoclonal antibodies directed against lymphocyte antigens and in patients with disease involvement of the bone marrow [see Adverse Reactions (6.1)].

Reactivation of hepatitis B virus infection was reported in 1% of patients in clinical trials. In patients with evidence of prior hepatitis B infection, consider monitoring for reactivation, and consider antiviral prophylaxis.

Reactivation of Epstein Barr viral infection leading to liver failure has occurred in recipients of ISTODAX including after ganciclovir prophylaxis.

5.3 Electrocardiographic Changes

Several treatment-emergent morphological changes in ECGs (including T-wave and ST-segment changes) have been reported in clinical studies. The clinical significance of these changes is unknown [see Adverse Reactions (6.1)].

In patients with congenital long QT syndrome, patients with a history of significant cardiovascular disease, and patients taking anti-arrhythmic medicines or medicinal products that lead to significant QT prolongation, consider cardiovascular monitoring of ECGs at baseline and periodically during treatment.

Confirm that potassium and magnesium levels are within normal range before administration of ISTODAX [see Adverse Reactions (6.1)].

5.4 Tumor Lysis Syndrome

Tumor lysis syndrome (TLS) has been reported to occur in recipients of ISTODAX, including in 1% of patients with tumor stage CTCL. Patients with advanced stage disease and/or high tumor burden are at greater risk, should be closely monitored, and managed as appropriate.

5.5 Embryo-Fetal Toxicity

Based on its mechanism of action and findings from animal studies, ISTODAX can cause fetal harm when administered to a pregnant woman. In an animal reproductive study, romidepsin was embryocidal and caused adverse developmental outcomes at exposures below those in patients at the recommended dose of 14 mg/m^2. Advise females of reproductive potential to use effective contraception during treatment and for 1 month after the last dose. Advise males with female partners of reproductive potential to use effective contraception during treatment and for 1 month after the last dose [see Use in Specific Populations (8.1, 8.3) and Clinical Pharmacology (12.1)].

6 ADVERSE REACTIONS

The following adverse reactions are described in more detail in other sections of the prescribing information.

- Myelosuppression [see Warnings and Precautions (5.1)]
- Infections [see Warnings and Precautions (5.2)]
- Electrocardiographic Changes [see Warnings and Precautions (5.3)]
- Tumor Lysis Syndrome [see Warnings and Precautions (5.4)]

6.1 Clinical Trials Experience

Because clinical trials are conducted under widely varying conditions, adverse reaction rates observed in the clinical trials of a drug cannot be directly compared to rates in the clinical trials of another drug and may not reflect the rates observed in practice.

The data in the WARNINGS AND PRECAUTIONS reflect exposure to ISTODAX in four clinical trials involving 363 patients with T-cell lymphoma, including 185 patients with CTCL. ISTODAX was administered as a single agent at a dosage of 14 mg/m^2 on days 1, 8, and 15 of a 28-day cycle. Among 363 patients who received ISTODAX, 21% were exposed for 6 months or longer and 13% were exposed for greater than one year.

Cutaneous T-Cell Lymphoma

The safety of ISTODAX was evaluated in 185 patients with CTCL in 2 single arm clinical studies in which patients received a dosage of 14 mg/m^2 on days 1, 8, and 15 of a 28-day cycle. Treatment continued as long as the patient benefitted from and tolerated the drug. The mean duration of treatment in these studies was 5.6 months (range: <1 to 83.4 months).

Common Adverse Reactions

Table 2 summarizes the most frequent adverse reactions (>20%) regardless of causality using the National Cancer Institute-Common Terminology Criteria for Adverse Events (NCI-CTCAE, Version 3.0). Due to methodological differences between the studies, the AE data are presented separately for Study 1 and Study 2. Adverse reactions are ranked by their incidence in Study 1. Laboratory abnormalities commonly reported (>20%) as adverse reactions are included in Table 2.

Table 2. Adverse Reactions Occurring in >20% of Patients in Either CTCL Study (N=185)
Adverse Reactions n (%) | Study 1 (n=102) |  | Study 2 (n=83)
Adverse Reactions n (%) | All grades | Grade 3 or 4 | All grades | Grade 3 or 4
Any adverse reactions | 99 (97) | 36 (35) | 83 (100) | 68 (82)
Nausea | 57 (56) | 3 (3) | 71 (86) | 5 (6)
Asthenia/Fatigue | 54 (53) | 8 (8) | 64 (77) | 12 (14)
Infections | 47 (46) | 11 (11) | 45 (54) | 27 (33)
Vomiting | 35 (34) | 1 (<1) | 43 (52) | 8 (10)
Anorexia | 23 (23) | 1 (<1) | 45 (54) | 3 (4)
Hypomagnesemia | 22 (22) | 1 (<1) | 23 (28) | 0
Diarrhea | 20 (20) | 1 (<1) | 22 (27) | 1 (1)
Pyrexia | 20 (20) | 4 (4) | 19 (23) | 1 (1)
Anemia | 19 (19) | 3 (3) | 60 (72) | 13 (16)
Thrombocytopenia | 17 (17) | 0 | 54 (65) | 12 (14)
Dysgeusia | 15 (15) | 0 | 33 (40) | 0
Constipation | 12 (12) | 2 (2) | 32 (39) | 1 (1)
Neutropenia | 11 (11) | 4 (4) | 47 (57) | 22 (27)
Hypotension | 7 (7) | 3 (3) | 19 (23) | 3 (4)
Pruritus | 7 (7) | 0 | 26 (31) | 5 (6)
Hypokalemia | 6 (6) | 0 | 17 (20) | 2 (2)
Dermatitis/Exfoliative dermatitis | 4 (4) | 1 (<1) | 22 (27) | 7 (8)
Hypocalcemia | 4 (4) | 0 | 43 (52) | 5 (6)
Leukopenia | 4 (4) | 0 | 38 (46) | 18 (22)
Lymphopenia | 4 (4) | 0 | 47 (57) | 31 (37)
Alanine aminotransferase increased | 3 (3) | 0 | 18 (22) | 2 (2)
Aspartate aminotransferase increased | 3 (3) | 0 | 23 (28) | 3 (4)
Hypoalbuminemia | 3 (3) | 1 (<1) | 40 (48) | 3 (4)
Electrocardiogram ST-T wave changes | 2 (2) | 0 | 52 (63) | 0
Hyperglycemia | 2 (2) | 2 (2) | 42 (51) | 1 (1)
Hyponatremia | 1 (<1) | 1 (<1) | 17 (20) | 2 (2)
Hypermagnesemia | 0 | 0 | 22 (27) | 7 (8)
Hypophosphatemia | 0 | 0 | 22 (27) | 8 (10)
Hyperuricemia | 0 | 0 | 27 (33) | 7 (8)

Serious Adverse Reactions

Infections were the most common type of SAE reported in both studies with 8 patients (8%) in Study 1 and 26 patients (31%) in Study 2 experiencing a serious infection. Serious adverse reactions reported in >2% of patients in Study 1 were sepsis and pyrexia (3%). In Study 2, serious adverse reactions in >2% of patients were fatigue (7%), supraventricular arrhythmia, central line infection, neutropenia (6%), hypotension, hyperuricemia, edema (5%), ventricular arrhythmia, thrombocytopenia, nausea, leukopenia, dehydration, pyrexia, aspartate aminotransferase increased, sepsis, catheter related infection, hypophosphatemia and dyspnea (4%).

There were eight deaths not due to disease progression. In Study 1, there were two deaths: one due to cardiopulmonary failure and one due to acute renal failure. There were six deaths in Study 2: four due to infection and one each due to myocardial ischemia and acute respiratory distress syndrome.

Discontinuations

Discontinuation due to an adverse event occurred in 21% of patients in Study 1 and 11% in Study 2. Discontinuations occurring in at least 2% of patients in either study included infection, fatigue, dyspnea, QT prolongation, and hypomagnesemia.

Other Clinical Trials Experience

The following common adverse reactions have been reported following administration of ISTODAX as a single agent in 178 patients with peripheral T-cell lymphoma, for which ISTODAX is not indicated or recommended. The most common adverse reactions (≥30%) included nausea (63%), fatigue (61%), thrombocytopenia (49%), vomiting (39%), neutropenia (39%), pyrexia (38%), diarrhea (36%) and anemia (35%). Other common (≥10%) clinically significant adverse reactions included dysgeusia (22%), headache (20%), cough (19%), dyspnea (15%), abdominal pain (13%) and stomatitis (10%). Grade 3 and higher adverse reactions in ≥10% were hematologic toxicities (including thrombocytopenia, neutropenia, leukopenia and anemia) and fatigue.

7 DRUG INTERACTIONS

7.1 Warfarin or Coumarin Derivatives

Prolongation of PT and elevation of INR were observed in a patient receiving ISTODAX concomitantly with warfarin. Monitor PT and INR more frequently in patients concurrently receiving ISTODAX and warfarin [see Clinical Pharmacology (12.3)].

7.2 Drugs That Inhibit CYP3A4 Enzymes

Strong CYP3A4 inhibitors increase concentrations of romidepsin [see Clinical Pharmacology (12.3)]. Monitor for toxicity related to increased romidepsin exposure and follow the dose modifications for toxicity [see Dosage and Administration (2.2)] when ISTODAX is initially co-administered with strong CYP3A4 inhibitors.

7.3 Drugs That Induce CYP3A4 Enzymes

Rifampin (a potent CYP3A4 inducer) increased the concentrations of romidepsin [see Clinical Pharmacology (12.3)]. Avoid co-administration of ISTODAX with rifampin. The use of other potent CYP3A4 inducers should be avoided when possible.

8 USE IN SPECIFIC POPULATIONS

8.1 Pregnancy

Risk Summary

Based on its mechanism of action and findings from animal studies, ISTODAX can cause embryo-fetal harm when administered to a pregnant woman [see Clinical Pharmacology (12.1)].

There are no available data on ISTODAX use in pregnant women to inform a drug associated risk of major birth defects and miscarriage. In an animal reproductive study, romidepsin was embryocidal and caused adverse developmental outcomes including embryo-fetal toxicity and malformations at exposures below those in patients at the recommended dose (see Data). Advise pregnant women of the potential risk to a fetus and to avoid becoming pregnant while receiving ISTODAX and for at least 1 month after the last dose.

The background risk of major birth defects and miscarriage for the indicated population is unknown. All pregnancies have a background risk of birth defect, loss, or other adverse outcomes. In the U.S. general population, the estimated background risk of major birth defects and miscarriage in clinically recognized pregnancies is 2-4% and 15-20%, respectively.

Data

Animal Data

Romidepsin was administered intravenously to pregnant rats during the period of organogenesis at doses of 0.1, 0.2, or 0.5 mg/kg/day. Substantial resorption or postimplantation loss was observed at the high dose of 0.5 mg/kg/day, a maternally toxic dose. Adverse embryo-fetal effects were noted at romidepsin doses of ≥0.1 mg/kg/day, with systemic exposures (AUC) ≥0.2% of the human exposure at the recommended dose of 14 mg/m^2/week. Drug-related fetal effects consisted of reduced fetal body weights, folded retina, rotated limbs, and incomplete sternal ossification.

8.2 Lactation

Risk Summary

There are no data on the presence of ISTODAX or its metabolites in human milk, the effects on the breastfed child, or the effects on milk production. Because many drugs are excreted in human milk and because of the potential for serious adverse reactions in the breastfed child, advise lactating women not to breastfeed during treatment with ISTODAX and for 1 week after the last dose.

8.3 Females and Males of Reproductive Potential

ISTODAX can cause fetal harm when administered to a pregnant woman [see Use in Specific Populations (8.1)].

Pregnancy Testing

Perform pregnancy testing in females of reproductive potential within 7 days prior to initiating therapy with ISTODAX.

Contraception

Females

Advise females of reproductive potential to use effective contraception during treatment with ISTODAX and for 1 month after the last dose. ISTODAX may reduce the effectiveness of estrogen-containing contraceptives. Therefore, alternative methods of non-estrogen containing contraception (e.g., condoms, intrauterine devices) should be used in patients receiving ISTODAX.

Males

Advise males with female partners of reproductive potential to use effective contraception during treatment with ISTODAX and for 1 month after the last dose.

Infertility

Based on findings in animals, romidepsin has the potential to affect male and female fertility [see Nonclinical Toxicology (13.1)].

8.4 Pediatric Use

The safety and effectiveness of ISTODAX in pediatric patients have not been established.

8.5 Geriatric Use

Of the 186 patients with CTCL who received ISTODAX in clinical studies, 51 (28%) were 65 years of age and older, while 16 (9%) were 75 years of age. No overall differences in safety or effectiveness were observed between patients 65 years or age and over and younger patients; however, greater sensitivity of some older individuals cannot be ruled out.

8.6 Hepatic Impairment

In a hepatic impairment study, ISTODAX was evaluated in 19 patients with advanced cancer and mild (8), moderate (5), or severe (6) hepatic impairment. There were 4 deaths during the first cycle of treatment: 1 patient with mild hepatic impairment, 1 patient with moderate hepatic impairment, and 2 patients with severe hepatic impairment. No dose adjustments are recommended for patients with mild hepatic impairment. Reduce the ISTODAX starting dose for patients with moderate and severe hepatic impairment [see Dosage and Administration (2.3) and Clinical Pharmacology (12.3)]. Monitor patients with hepatic impairment more frequently for toxicity, especially during the first cycle of therapy.

10 OVERDOSAGE

No specific information is available on the treatment of overdosage of ISTODAX.

Toxicities in a single-dose study in rats or dogs, at intravenous romidepsin doses up to 2.2-fold the recommended human dose based on the body surface area, included irregular respiration, irregular heartbeat, staggering gait, tremor, and tonic convulsions.

In the event of an overdose, it is reasonable to employ the usual supportive measures, e.g., clinical monitoring and supportive therapy, if required. There is no known antidote for ISTODAX and it is not known if ISTODAX is dialyzable.

11 DESCRIPTION

Romidepsin, a histone deacetylase (HDAC) inhibitor, is a bicyclic depsipeptide. At room temperature, romidepsin is a white powder and is described chemically as (1S,4S,7Z,10S,16E,21R)-7-ethylidene-4,21-bis(1-methylethyl)-2-oxa-12,13-dithia-5,8,20,23-tetraazabicyclo[8.7.6]tricos-16-ene-3,6,9,19,22-pentone. The empirical formula is C24H36N4O6S2.

The molecular weight is 540.71 and the structural formula is:

ISTODAX (romidepsin) for injection is intended for intravenous infusion only after reconstitution with the supplied diluent and after further dilution with 0.9% Sodium Chloride, USP.

ISTODAX is supplied as a kit containing 2 vials.

ISTODAX (romidepsin) for injection is a sterile lyophilized white powder and is supplied in a 10 mg single-dose vial containing 11 mg romidepsin, 22 mg povidone, USP, and hydrochloric acid, NF, as a pH adjuster.

Diluent for ISTODAX is a sterile clear solution and is supplied in a single-dose vial containing 2.4 mL (2.2 mL deliverable volume). Diluent for ISTODAX contains 80% (v/v) propylene glycol, USP and 20% (v/v) dehydrated alcohol, USP.

12 CLINICAL PHARMACOLOGY

12.1 Mechanism of Action

Romidepsin is a histone deacetylase (HDAC) inhibitor. HDACs catalyze the removal of acetyl groups from acetylated lysine residues in histones, resulting in the modulation of gene expression. HDACs also deacetylate non-histone proteins, such as transcription factors. In vitro, romidepsin causes the accumulation of acetylated histones, and induces cell cycle arrest and apoptosis of some cancer cell lines with IC50 values in the nanomolar range. The mechanism of the antineoplastic effect of romidepsin observed in nonclinical and clinical studies has not been fully characterized.

12.2 Pharmacodynamics

Cardiac Electrophysiology

At doses of 14 mg/m^2 as a 4-hour intravenous infusion, and at doses of 8 (0.57 times the recommended dose), 10 (0.71 times the recommended dose) or 12 (0.86 times the recommended dose) mg/m^2 as a 1-hour infusion, no large changes in the mean QTc interval (>20 milliseconds) from baseline based on Fridericia correction method were detected. Small increase in mean QT interval (< 10 milliseconds) and mean QT interval increase between 10 to 20 milliseconds cannot be excluded.

Romidepsin was associated with a delayed concentration-dependent increase in heart rate in patients with advanced cancer with a maximum mean increase in heart rate of 20 beats per minute occurring at the 6-hour time point after start of romidepsin infusion for patients receiving 14 mg/m^2 as a 4-hour infusion.

12.3 Pharmacokinetics

In patients with T-cell lymphomas who received 14 mg/m^2 of romidepsin intravenously over a 4-hour period on days 1, 8, and 15 of a 28-day cycle, geometric mean values of the maximum plasma concentration (Cmax) and the area under the plasma concentration versus time curve (AUC0-∞) were 377 ng/mL and 1549 ng*hr/mL, respectively. Romidepsin exhibited linear pharmacokinetics across doses ranging from 1.0 (0.07 times the recommended dose) to 24.9 (1.76 times the recommended dose) mg/m^2 when administered intravenously over 4 hours in patients with advanced cancers.

Distribution

Romidepsin is highly protein bound in plasma (92% to 94%) over the concentration range of 50 ng/mL to 1000 ng/mL with α1-acid-glycoprotein (AAG) being the principal binding protein. Romidepsin is a substrate of the efflux transporter P-glycoprotein (P-gp, ABCB1).

In vitro, romidepsin accumulates into human hepatocytes via an unknown active uptake process. Romidepsin is not a substrate of the following uptake transporters: BCRP, BSEP, MRP2, OAT1, OAT3, OATP1B1, OATP1B3, or OCT2. In addition, romidepsin is not an inhibitor of BCRP, MRP2, MDR1 or OAT3. Although romidepsin did not inhibit OAT1, OCT2, and OATP1B3 at concentrations seen clinically (1 μmol/L), modest inhibition was observed at 10 µmol/L. Romidepsin was found to be an inhibitor of BSEP and OATP1B1.

Metabolism

Romidepsin undergoes extensive metabolism in vitro primarily by CYP3A4 with minor contribution from CYP3A5, CYP1A1, CYP2B6, and CYP2C19. At therapeutic concentrations, romidepsin did not competitively inhibit CYP1A2, CYP2C9, CYP2C19, CYP2D6, CYP2E1, or CYP3A4 in vitro.

At therapeutic concentrations, romidepsin did not cause notable induction of CYP1A2, CYP2B6 and CYP3A4 in vitro. Therefore, pharmacokinetic drug-drug interactions are unlikely to occur due to CYP450 induction or inhibition by romidepsin when co-administered with CYP450 substrates.

Excretion

Following 4-hour intravenous administration of romidepsin at 14 mg/m^2 on days 1, 8, and 15 of a 28-day cycle in patients with T-cell lymphomas, the terminal half-life (t½) was approximately 3 hours. No accumulation of plasma concentration of romidepsin was observed after repeated dosing.

Drug Interactions

Ketoconazole: Following co-administration of 8 mg/m^2 ISTODAX (4-hour infusion) with ketoconazole, the overall romidepsin exposure was increased by approximately 25% and 10% for AUC0-∞ and Cmax, respectively, compared to romidepsin alone, and the difference in AUC0-∞ between the 2 treatments was statistically significant.

Rifampin: Following co-administration of 14 mg/m^2 ISTODAX (4-hour infusion) with rifampin, the overall romidepsin exposure was increased by approximately 80% and 60% for AUC0-∞ and Cmax, respectively, compared to romidepsin alone, and the difference between the 2 treatments was statistically significant. Co-administration of rifampin decreased the romidepsin clearance and volume of distribution by 44% and 52%, respectively. The increase in exposure seen after co-administration with rifampin is likely due to rifampin's inhibition of an undetermined hepatic uptake process that is predominant for the disposition of ISTODAX.

Drugs that inhibit P-glycoprotein: Drugs that inhibit p-glycoprotein may increase the concentration of romidepsin.

Specific Populations

Effect of Age, Gender, Race or Renal Impairment

The pharmacokinetics of romidepsin was not influenced by age (27 to 83 yrs), gender, race (white vs. black) or mild (estimated creatinine clearance 50 - 80 mL/min), moderate (estimated creatinine clearance 30-50 mL/min), or severe (estimated creatinine clearance <30 mL/min) renal impairment. The effect of end-stage renal disease (estimated creatine clearance less than 15 mL/min) on romidepsin pharmacokinetics has not been studied.

Hepatic Impairment

Romidepsin clearance decreased with increased severity of hepatic impairment. In patients with cancer, the geometric mean Cmax values after administration of 14, 7, and 5 mg/m^2 romidepsin in patients with mild (B1: bilirubin ≤ULN and AST >ULN; B2: bilirubin >ULN but ≤1.5 × ULN and any AST), moderate (bilirubin >1.5 × ULN to ≤3 × ULN and any AST), and severe (bilirubin >3 × ULN and any AST) hepatic impairment were approximately 111%, 96%, and 86% of the corresponding value after administration of 14 mg/m^2 romidepsin in patients with normal (bilirubin ≤upper limit of normal (ULN) and aspartate aminotransferase (AST) ≤ULN) hepatic function, respectively. The geometric mean AUCinf values in patients with mild, moderate, and severe hepatic impairment were approximately 144%, 114%, and 116% of the corresponding value in patients with normal hepatic function, respectively. Among these 4 cohorts, moderate interpatient variability was noted for the exposure parameters Cmax and AUCinf, as the coefficient of variation (CV) ranged from 30% to 54%.

13 NONCLINICAL TOXICOLOGY

13.1 Carcinogenesis, Mutagenesis, Impairment of Fertility

Carcinogenicity studies have not been performed with romidepsin. Romidepsin was not mutagenic in vitro in the bacterial reverse mutation assay (Ames test) or the mouse lymphoma assay. Romidepsin was not clastogenic in an in vivo rat bone marrow micronucleus assay when tested to the maximum tolerated dose (MTD) of 1 mg/kg in males and 3 mg/kg in females (6 and 18 mg/m^2 in males and females, respectively). These doses were up to 1.3-fold the recommended human dose, based on body surface area.

Based on nonclinical findings, male and female fertility may be compromised by treatment with ISTODAX. In a 26-week toxicology study, romidepsin administration resulted in testicular degeneration in rats at 0.33 mg/kg/dose (2 mg/m^2/dose) following the clinical dosing schedule. This dose resulted in AUC0-∞ values that were approximately 2% the exposure level in patients receiving the recommended dose of 14 mg/m^2/dose. A similar effect was seen in mice after 4 weeks of drug administration at higher doses. Seminal vesicle and prostate organ weights were decreased in a separate study in rats after 4 weeks of daily drug administration at 0.1 mg/kg/day (0.6 mg/m^2/day), approximately 30% the estimated human daily dose based on body surface area. Romidepsin showed high affinity for binding to estrogen receptors in pharmacology studies. In a 26-week toxicology study in rats, atrophy was seen in the ovary, uterus, vagina and mammary gland of females administered doses as low as 0.1 mg/kg/dose (0.6 mg/m^2/dose) following the clinical dosing schedule. This dose resulted in AUC0-∞ values that were 0.3% of those in patients receiving the recommended dose of 14 mg/m^2/dose. Maturation arrest of ovarian follicles and decreased weight of ovaries were observed in a separate study in rats after 4 weeks of daily drug administration at 0.1 mg/kg/day (0.6 mg/m^2/day). This dose is approximately 30% the estimated human daily dose based on body surface area.

14 CLINICAL STUDIES

ISTODAX was evaluated in 2 multicenter, single-arm clinical studies in patients with CTCL (Study 1 [NCT00106431] and Study 2 [NCT00007345]). Overall, 167 patients with CTCL were treated in the US, Europe, and Australia. Study 1 included 96 patients with confirmed CTCL after failure of at least 1 prior systemic therapy. Study 2 included 71 patients with a primary diagnosis of CTCL who received at least 2 prior skin directed therapies or one or more systemic therapies. Patients were treated with ISTODAX at a starting dose of 14 mg/m^2 infused over 4 hours on days 1, 8, and 15 every 28 days.

In both studies, patients could be treated until disease progression at the discretion of the investigator and local regulators. Objective disease response was evaluated according to a composite endpoint that included assessments of skin involvement, lymph node and visceral involvement, and abnormal circulating T-cells ("Sézary cells").

The primary efficacy endpoint for both studies was overall objective disease response rate (ORR) based on the investigator assessments, and was defined as the proportion of patients with confirmed complete response (CR) or partial response (PR). CR was defined as no evidence of disease and PR as ≥ 50% improvement in disease. Secondary endpoints in both studies included duration of response and time to response.

Baseline Patient Characteristics

Demographic and disease characteristics of the patients in Study 1 and Study 2 are provided in Table 3.

Table 3. Baseline Patient Characteristics (CTCL Population)
Characteristic | Study 1 (N=96) | Study 2 (N=71)
Age
N | 96 | 71
Mean (SD) | 57 (12) | 56 (13)
Median (Range) | 57 (21, 89) | 57 (28, 84)
Sex, n (%)
Men | 59 (61) | 48 (68)
Women | 37 (39) | 23 (32)
Race, n (%)
White | 90 (94) | 55 (77)
Black | 5 (5) | 15 (21)
Other/Not Reported | 1 (1) | 1 (1)
Stage of Disease at Study Entry, n (%)
IA | 0 (0) | 1 (1)
IB | 15 (16) | 6 (9)
IIA | 13 (14) | 2 (3)
IIB | 21 (22) | 14 (20)
III | 23 (24) | 9 (13)
IVA | 24 (25) | 27 (38)
IVB | 0 (0) | 12 (17)
Number of Prior Skin-Directed Therapies
Median (Range) | 2 (0, 6) | 1 (0, 3)
Number of Prior Systemic Therapies
Median (Range) | 2 (1, 8) | 2 (0, 7)

Clinical Results

Efficacy outcomes for CTCL patients are provided in Table 4. Median time to first response was 2 months (range 1 to 6) in both studies. Median time to CR was 4 months in Study 1 and 6 months in Study 2 (range 2 to 9).

Table 4. Clinical Results for CTCL Patients
Response Rate | Study 1 (N=96) | Study 2 (N=71)
ORR (CR + PR), n (%) [95% Confidence Interval] | 33 (34) [25, 45] | 25 (35) [25, 49]
CR, n (%) [95% Confidence Interval] | 6 (6) [2, 13] | 4 (6) [2, 14]
PR, n (%) [95% Confidence Interval] | 27 (28) [19, 38] | 21 (30) [20, 43]
Duration of Response (months)
N | 33 | 25
Median (range) | 15 (1, 20*) | 11 (1, 66*)
*Denotes censored value.

15 REFERENCES

1. OSHA Hazardous Drugs. OSHA. [Accessed on 09/11/2018, from http://www.osha.gov/SLTC/hazardousdrugs/index.html]

16 HOW SUPPLIED/STORAGE AND HANDLING

How Supplied

ISTODAX is supplied as a kit including a sterile, lyophilized powder in a 10 mg single-dose vial containing 11 mg of romidepsin, 22 mg of the bulking agent, povidone, USP, and hydrochloric acid, NF, as a pH adjuster. In addition, each kit includes a single-dose sterile diluent vial containing 2.4 mL (2.2 mL deliverable volume) of 80% propylene glycol, USP, and 20% dehydrated alcohol, USP.

NDC 59572-984-01: ISTODAX® KIT containing 1 vial of romidepsin and 1 vial of diluent for romidepsin per carton.

Storage and Handling

ISTODAX (romidepsin) for injection is supplied as a kit containing 2 vials in a single carton. The carton must be stored at 20° to 25°C, excursions permitted between 15° to 30°C. (See USP Controlled Room Temperature.)

ISTODAX is a hazardous drug. Follow applicable special handling and disposal procedures.^1

17 PATIENT COUNSELING INFORMATION

Advise the patient to read the FDA-approved patient labeling (Patient Information).

Low Blood Counts

Advise patients that treatment with ISTODAX can cause low blood counts and that frequent monitoring of hematologic parameters is required. Patients should be instructed to report fever or other signs of infection, significant fatigue, shortness of breath, or bleeding [see Warnings and Precautions (5.1)].

Infections

Advise patients that infections may occur during treatment with ISTODAX. Advise patients to report fever, cough, shortness of breath with or without chest pain, burning on urination, flu-like symptoms, muscle aches, or worsening skin problems. Advise patients to report any previous history of hepatitis B before starting romidepsin [see Warnings and Precautions (5.2)].

Tumor Lysis Syndrome

Advise patients of the risk of tumor lysis syndrome (especially those with advanced stage disease and/or high tumor burden) to maintain high fluid intake for at least 72 hours after each dose [see Warnings and Precautions (5.4)].

Nausea and Vomiting

Advise patients that nausea and vomiting are common following treatment with ISTODAX. Prophylactic antiemetics are recommended for all patients. Advise patients to report these symptoms so that appropriate treatment can be instituted [see Adverse Reactions (6.1)].

Embryo-Fetal Toxicity

Advise patients that ISTODAX can cause fetal harm when administered during pregnancy [see Warnings and Precautions (5.5) and Use in Specific Populations (8.1)].

Contraception

Advise females of reproductive potential to use effective contraception during treatment with ISTODAX and for 1 month after the last dose. Advise males with female partners of reproductive potential to use effective contraception during treatment with ISTODAX and for 1 month after the last dose [Use in Specific Populations (8.3)].

Lactation

Advise lactating women not to breastfeed during treatment with ISTODAX and for 1 week after the last dose [see Use in Specific Populations (8.2)].

Infertility

Advise females and males of reproductive potential that ISTODAX may cause infertility [see Nonclinical Toxicology (13.1)].

Marketed by:
Bristol-Myers Squibb Company
Princeton, NJ 08543 USA

ISTODAX® is a trademark of Celgene Corporation, a Bristol-Myers Squibb company.

ISTBAXPI.011/PPI.011

PATIENT INFORMATION
ISTODAX (ISS toe dax)
(romidepsin)
for injection

What is ISTODAX?
ISTODAX is a prescription medicine used to treat people with a type of cancer called cutaneous T-cell lymphoma (CTCL) after at least one other type of medicine by mouth or injection has been tried.
It is not known if ISTODAX is safe and effective in children under 18 years of age.

Before receiving ISTODAX, tell your healthcare provider about all of your medical conditions, including if you:

- have any heart problems, including an irregular or fast heartbeat, or a condition called QT prolongation.
- have kidney problems
- have liver problems, including a history of hepatitis B
- have problems with the amount of potassium or magnesium in your blood
- have nausea, vomiting, or diarrhea
- are pregnant or plan to become pregnant. ISTODAX may harm your unborn baby.
  - Females who are able to become pregnant:
    - Your healthcare provider will perform a pregnancy test within 7 days before you start treatment with ISTODAX.
    - You should avoid becoming pregnant during treatment with ISTODAX and for 1 month after the last dose.
    - You should use effective birth control (contraception) during treatment with ISTODAX and for 1 month after your last dose.
    - ISTODAX may affect the way estrogen-containing birth control works. Talk to your healthcare provider for more information about other types of birth control to use during treatment with ISTODAX.
    - Tell your healthcare provider right away if you become pregnant or think you may be pregnant during treatment with ISTODAX.
  - Males with a female sexual partner who can become pregnant:
    - ISTODAX can harm the unborn baby of your partner.
    - You should use a condom and avoid fathering a child during treatment with ISTODAX and for 1 month after treatment with ISTODAX. Talk to your healthcare provider if this is a concern for you.
  - ISTODAX may cause fertility problems in males and females. Talk to your healthcare provider if this is a concern for you.
- are breastfeeding or plan to breastfeed. It is not known if ISTODAX passes into your breast milk. You should not breastfeed during treatment with ISTODAX and for 1 week after the last dose. Talk to your healthcare provider about the best way to feed your baby while you are being treated with ISTODAX.

Tell your healthcare provider about all of the medicines you take, including prescription and over-the-counter medicines, vitamins, and herbal supplements.
Some medicines may affect how ISTODAX works, or ISTODAX may affect how other medicines work. Especially tell your healthcare provider if you take or use:

- warfarin sodium (Coumadin, Jantoven) or any other blood thinner medicine. Ask your healthcare provider if you are not sure if you are taking a blood thinner. Your healthcare provider may want to test your blood more often.
- a medicine to treat abnormal heartbeats
- St. John's wort (Hypericum perforatum)
- Dexamethasone (a steroid)
- Medicine for:
  - tuberculosis (TB)
  - seizures (epilepsy)
  - bacterial infections (antibiotics)
  - fungal infections (antifungals)
  - HIV (AIDS)
  - depression

Know the medicines you take. Keep a list of them and show it to your healthcare provider and pharmacist when you get a new medicine.

How will I receive ISTODAX?

- ISTODAX will be given to you by your healthcare provider or nurse as an intravenous injection into your vein usually over 4 hours.
- ISTODAX is usually given on Day 1, Day 8, and Day 15 of a 28-day cycle of treatment.
- Your healthcare provider will decide how long you will receive treatment with ISTODAX.
- Your healthcare provider will check your blood cell counts and other blood tests regularly during your treatment with ISTODAX to check for side effects of ISTODAX. Your healthcare provider may decide to do other tests to check your health as needed.
- Your healthcare provider may stop your treatment, change when you get your treatment, or change the dose of your treatment if you have certain side effects while receiving ISTODAX.

What are the possible side effects of ISTODAX?
ISTODAX may cause serious side effects, including:

- Low blood cell counts: Your healthcare provider will regularly do blood tests to check your blood counts.
  - Low platelets: can cause unusual bleeding or bruising under the skin. Talk to your healthcare provider right away if this happens.
  - Low red blood cells: may make you feel tired and you may get tired easily. You may look pale and feel short of breath. Tell your healthcare provider if you have these symptoms.
  - Low white blood cells: can cause you to get infections, which may be serious.
- Serious infections. People receiving ISTODAX can develop serious infections that can sometimes lead to death. These infections can happen during and after treatment with ISTODAX. Your risk of infection may be higher if you have had chemotherapy in the past. Tell your healthcare provider right away if you have any of these symptoms of infection:

- Fever
- cough
- shortness of breath with or without chest pain

- burning with urination
- flu-like symptoms
- muscle aches
- worsening skin problems

- Changes in your heartbeat. Your healthcare provider may check your heart by doing an ECG (electrocardiogram) and blood tests to check your potassium and magnesium levels, before you start ISTODAX treatment. Tell your healthcare provider if you feel an abnormal heartbeat, feel dizzy or faint, have chest pain or shortness of breath.
- Tumor Lysis Syndrome (TLS). TLS is a problem of the rapid breakdown of cancer cells that can happen during your treatment with ISTODAX. You should drink plenty of fluids in the 3 days after you receive treatment with ISTODAX. Your healthcare provider may do blood tests to check for TLS and may give you medicine to prevent or treat TLS.

The most common side effects of ISTODAX include:

- nausea, tiredness, vomiting, loss of appetite, changes in sense of taste, constipation, and itching.

These are not all the possible side effects of ISTODAX. Call your doctor for medical advice about side effects. You may report side effects to FDA at 1-800-FDA-1088.

General information about the safe and effective use of ISTODAX
Medicines are sometimes prescribed for purposes other than those listed in a Patient Information leaflet.
This Patient Information leaflet summarizes the most important information about ISTODAX. If you would like more information, talk with your healthcare provider. You can ask your pharmacist or healthcare provider for information about ISTODAX that is written for health professionals.

What are the ingredients in ISTODAX?
Active ingredient: romidepsin
Inactive ingredients: povidone, hydrochloric acid as a pH adjuster. The diluent contains 80% propylene glycol and 20% dehydrated alcohol.

Marketed by:

Bristol-Myers Squibb Company
Princeton, NJ 08543 USA

ISTODAX® is a trademark of Celgene Corporation, a Bristol-Myers Squibb company.
ISTBAXPPI.011 1/23
For more information, go to www.ISTODAX.com or call 1-800-721-5072.

This Patient Information has been approved by the U.S. Food and Drug Administration.

Revised: January 2023

PRINCIPAL DISPLAY PANEL - Kit Carton

NDC 59572-984-01

ISTODAX® Kit
(romidepsin) for injection

10 mg/vial

Rx Only

Reconstitution and dilution required.

Each kit contains:

— One 10 mg single-dose vial of ISTODAX®
— One single-dose vial with 2.2 mL of Diluent

For Intravenous Use Only

Single-Dose Vial - Discard Unused Portion

Product of Germany

PRINCIPAL DISPLAY PANEL - 10 mg Vial Label

NDC 59572-962-10

ISTODAX®
(romidepsin) for injection

Rx Only

10 mg/vial

FOR INTRAVENOUS USE ONLY.

Directions For Use: See accompanying package
insert for complete reconstitution directions.
Product MUST be reconstituted with 2.2 mL
of supplied Diluent for a concentration of
5 mg/mL and then further diluted in 500 mL
of 0.9% sodium chloride injection, USP.

PRINCIPAL DISPLAY PANEL - 2.2 mL Vial Label

DILUENT
for ISTODAX®

NDC 59572-973-02

Rx Only

2.2 mL per single-dose vial
Each vial contains 80% propylene glycol and 20% dehydrated
alcohol. Dosage and Administration: Withdraw 2.2 mL
of Diluent to reconstitute 10 mg vial of ISTODAX®.

LOT:

EXP: